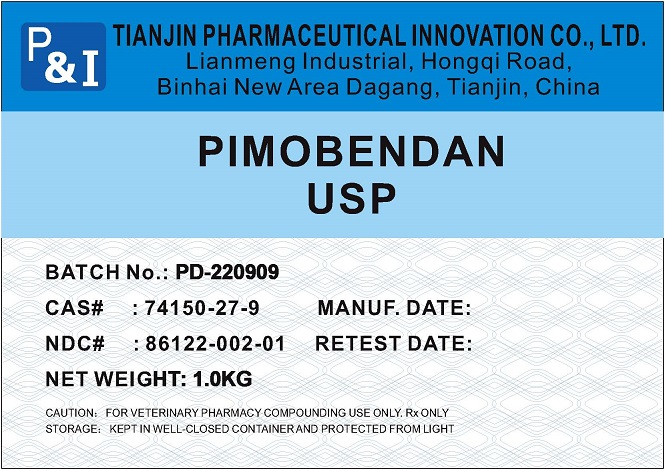 DRUG LABEL: Pimobendan
NDC: 86122-002 | Form: POWDER
Manufacturer: Tianjin Pharmaceutical Innovation Co.,Ltd.
Category: other | Type: BULK INGREDIENT - ANIMAL DRUG
Date: 20230104

ACTIVE INGREDIENTS: PIMOBENDAN 1 kg/1 kg

Pimobendan

PRINCIPAL DISPLAY PANEL – BULK PRODUCT

PIMOBENDANLISTING(2).jpg